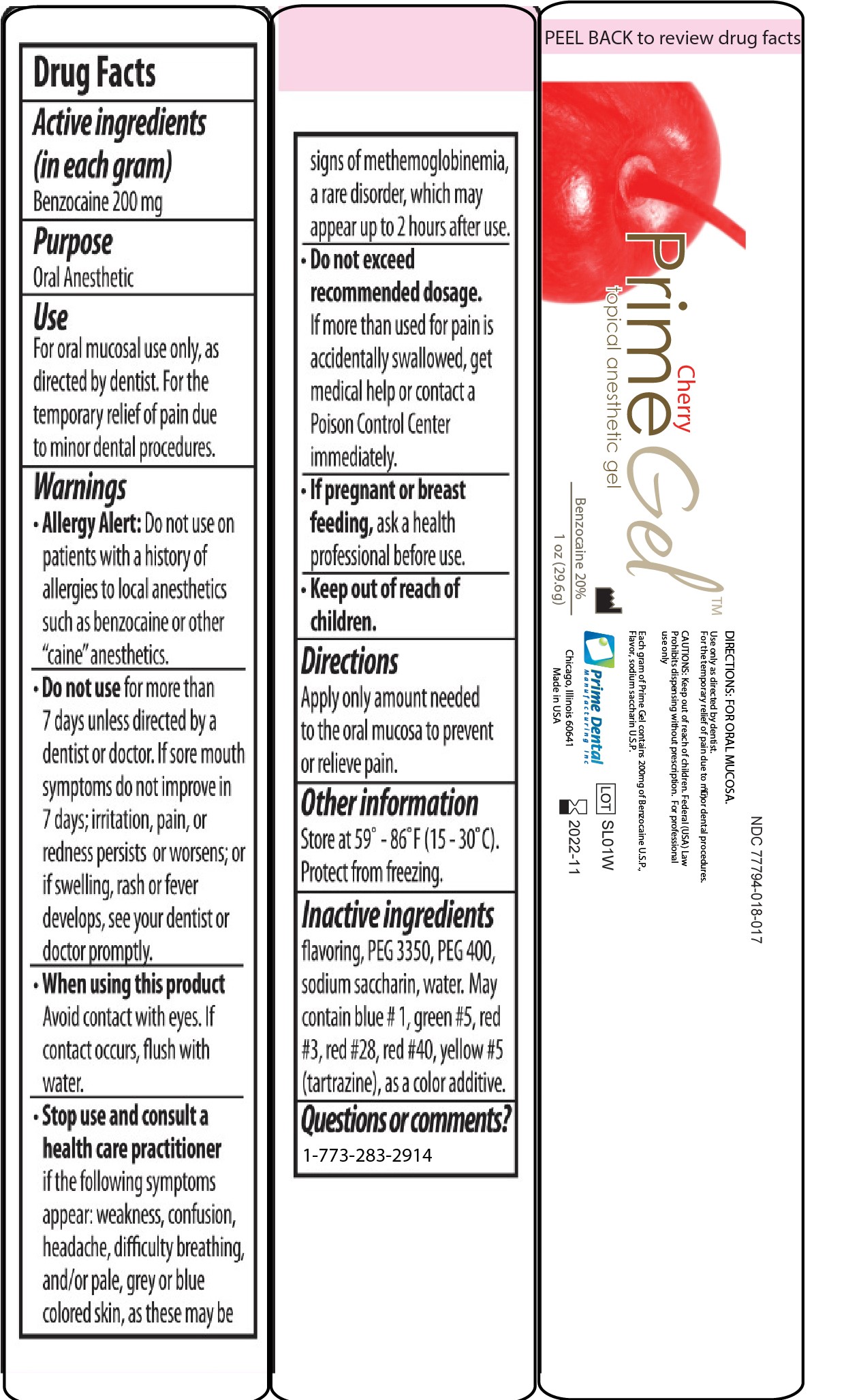 DRUG LABEL: Prime-Gel
NDC: 77794-018 | Form: GEL
Manufacturer: Prime Dental Manufacturing, Inc.
Category: otc | Type: HUMAN OTC DRUG LABEL
Date: 20251020

ACTIVE INGREDIENTS: BENZOCAINE 0.2 g/1 g
INACTIVE INGREDIENTS: POLYETHYLENE GLYCOL 400 0.69 g/1 g; HC RED NO. 3 0.0006 g/1 g; SACCHARIN 0.045 g/1 g; POLYETHYLENE GLYCOL 3350 0.05 g/1 g

DOSAGE AND ADMINISTRATION

Use for Oral mucosal use only, as directed by dentist. For the temporary relief of pain due to minor dental procedures.

Do not use for more than 7 days unless directed by a dentist or doctor.

See drug facts.

List of Inactive Ingredients

Flavoring, PEG3350, PEG400, sodium saccharin, water. may contain blue#, green #5, red #3, red #28, red#40, yellow #5 as color additives.

INDICATIONS AND USAGE

Use: for Oral mucosal use only, as directed by dentist. For the temporary relief of pain due to minor dental procedures.

Indications/Directions: Apply only amount needed to the oral mucosa to prevent or relieve pain.

See drug facts.

Keep out of reach section.

See drug facts:

Purpose: Oral Anesthetic.

See drug facts.

ACTIVE INGREDIENT

Active Ingridient: Benzocaine 0.2 g (200mg) per gram.

See drug facts.

Warnings

Allergy Alert: Do not use on patients with a history of allergies to local anesthetics such as benzocaine or other "caine" anesthetics.

Do not use for more than 7 days unless directed by a dentist or doctor. if sore mouth symptoms do not improve in 7 days; irritation, pain, or redness persists or worsens; or if swelling, rash or fever develops, see your dentist or doctor promptly.

When using this product avoid contact with eyes. If contact occures, flush with water.

Stop use and consult a health care practitioner if the following symptoms appear: weakness, confusion, headache, difficulty breathing, and/or pale, grey or blue colored skin, as these may be signs of methemoglobinemia, a rare disorder, which may appear up to 2 hours after use.

Do not exceed recommended dosage. If more than used for pain is accidentally swaloowed, get medical help or contact a posion control center immediately.

If pregnant or breast feeding, ask a health care proffesional before use.

Keep out of reach of children.

QUESTIONS

Contact 773-283-2914

PREGNANCY OR BREAST FEEDING

If pregnant or breast feeding ask a health care professional before use.

Stop use and consult a health care practitioner if the following symptoms appear: weakness, confusion, headache, difficulty breathing, and/or pale, grey or blue colored skin, as these may be signs of methemoglobinemia, a rare disorder, which may appear up to 2 hours after use.

Warnings

Allergy Alert: Do not use on patients with a history of allergies to local anesthetics such as benzocaine or other "caine" anesthetics.

Do not use for more than 7 days unless directed by a dentist or doctor. if sore mouth symptoms do not improve in 7 days; irritation, pain, or redness persists or worsens; or if swelling, rash or fever develops, see your dentist or doctor promptly.

When using this product avoid contact with eyes. If contact occures, flush with water.

Stop use and consult a health care practitioner if the following symptoms appear: weakness, confusion, headache, difficulty breathing, and/or pale, grey or blue colored skin, as these may be signs of methemoglobinemia, a rare disorder, which may appear up to 2 hours after use.

Do not exceed recommended dosage. If more than used for pain is accidentally swaloowed, get medical help or contact a posion control center immediately.

If pregnant or breast feeding, ask a health care proffesional before use.

Keep out of reach of children.